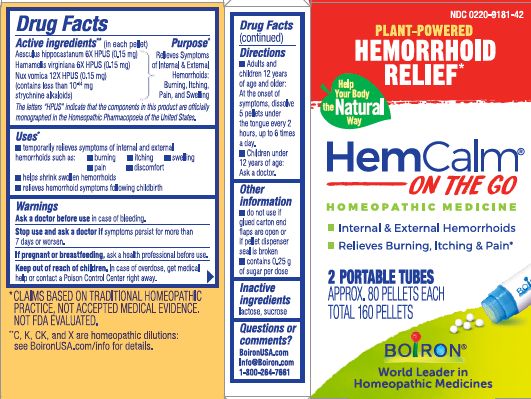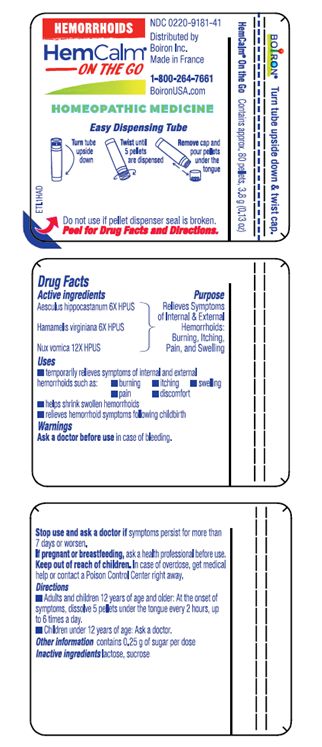 DRUG LABEL: HEMCALM
NDC: 0220-9181 | Form: PELLET
Manufacturer: Boiron
Category: homeopathic | Type: HUMAN OTC DRUG LABEL
Date: 20230213

ACTIVE INGREDIENTS: STRYCHNOS NUX-VOMICA SEED 12 [hp_X]/1 1; HORSE CHESTNUT 6 [hp_X]/1 1; HAMAMELIS VIRGINIANA ROOT BARK/STEM BARK 6 [hp_X]/1 1
INACTIVE INGREDIENTS: LACTOSE, UNSPECIFIED FORM; SUCROSE

HemCalm Pellets

Active Ingredient** (in each pellet)

Aesculus hippocastanum 6X HPUS (0.15 mg)

Hamamelis virginiana 6X HPUS (0.15 mg)

Nux Vomica 12X HPUS (0.15 mg) (contains less than 10-14 mg strychnine alkaloids)

The letters "HPUS" indicate that the components in this product are officially monographed in the Homeopathic Pharmacopoeia of the United States.

Purpose*

Relieves Symptoms of Internal & External Hemorrhoids: Burning, Itching, Pain, and Swelling

Uses*

- temporarily relieves symptoms of internal and external hemorrhoids such as:
- burning
- itching
- swelling
- pain
- discomfort
- helps shrink swollen hemorrhoids
- relieves hemorrhoid symptoms following childbirth

Ask a doctor before use in case of bleeding.

Stop use and ask a doctor if symptoms persist for more than 7 days or worsen.

PREGNANCY OR BREAST FEEDING

If pregnant or breastfeeding, ask a health professional before use.

Keep out of reach of children. In case of overdose, get medical help or contact a Poison Control Center right away.

DOSAGE AND ADMINISTRATION

- Adults and children 12 years of age and older: At the onset of symptoms, dissolve 5 pellets under the tongue every 2 hours, up to 6 times a day.
- Children under 12 years of age: Ask a doctor.

- do not use if glued carton end flaps are open or if pellet dispenser seal is broken
- contains 0.25 g of sugar per dose

Hemorrhoid Relief*

Internal & External Hemorrhoids

Relieves Burning, Itching & Pain*

2 PORTABLE TUBES

APPROX. 80 PELLETS EACH

TOTAL 160 PELLETS

Contains 80 pellets, 3.8 g (0.13 oz)

Turn tube upside down, Twist until 5 pellets are dispensed, Remove cap and pour pellets under the tongue

Do not use if pellet dispenser seal is broken.

*CLAIMS BASED ON TRADITIONAL HOMEOPATHIC PRACTICE NOT ACCEPTED MEDICAL EVIDENCE. NOT FDA EVALUATED.
**C,K,CK, and X are homeopathic dilutions: see BoironUSA.com/info for details.

INACTIVE INGREDIENT

lactose, sucrose

QUESTIONS

BoironUSA.com

Info@Boiron.com

1-800-264-7661

Made in France

Distributed by

Boiron, Inc.

Newtown Square, PA

19073